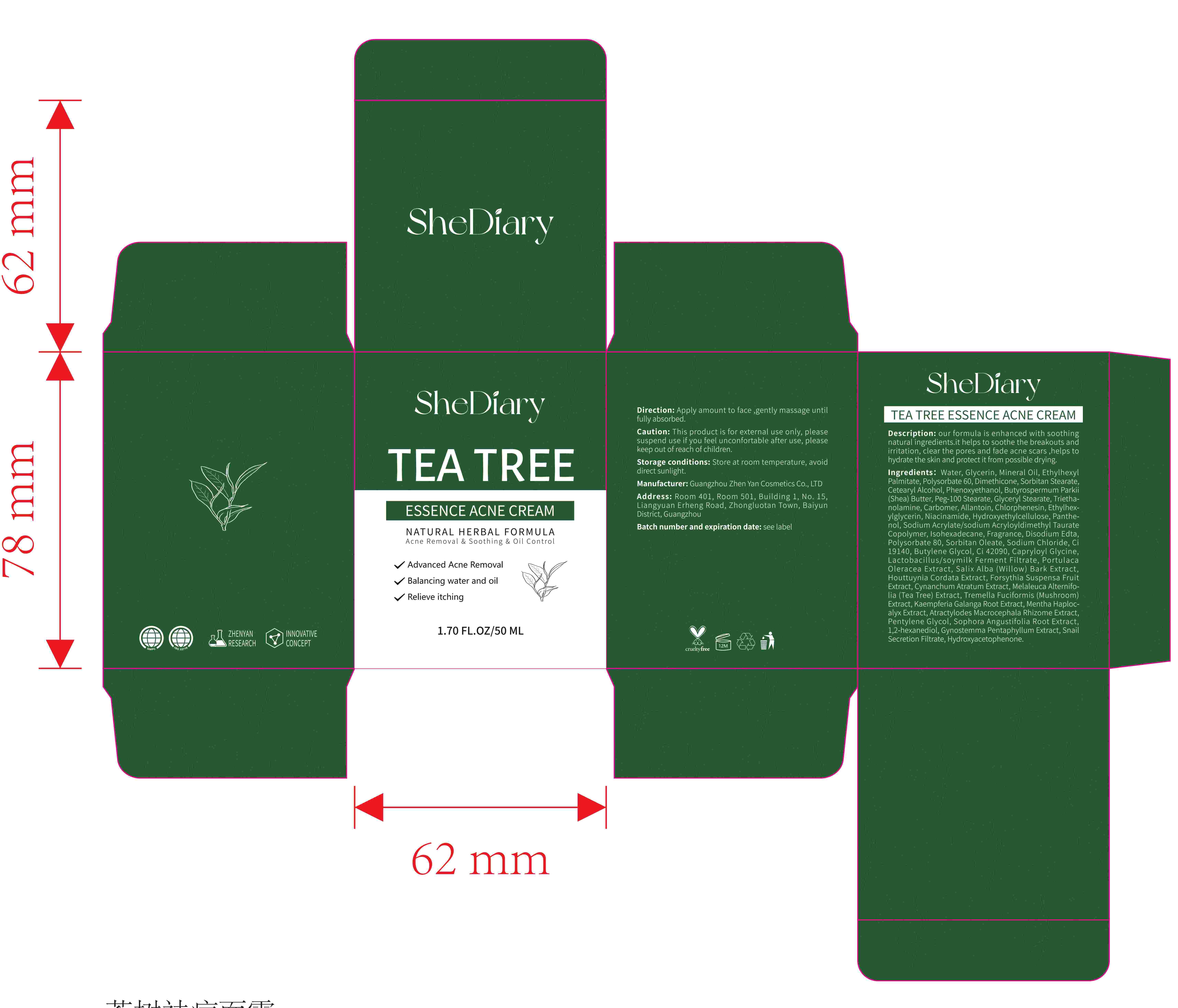 DRUG LABEL: shediary tea tree essence acne cream
NDC: 84372-018 | Form: LIQUID
Manufacturer: Shenzhen Zhumeng Times Technology Co., Ltd.
Category: otc | Type: HUMAN OTC DRUG LABEL
Date: 20240823

ACTIVE INGREDIENTS: NIACINAMIDE 10 g/100 mL
INACTIVE INGREDIENTS: GLYCERYL MONOSTEARATE; SODIUM CHLORIDE; ALLANTOIN; PENTYLENE GLYCOL; SALIX ALBA BARK; HOUTTUYNIA CORDATA FLOWERING TOP; WATER; GLYCERIN; POLYSORBATE 80; FD&C YELLOW NO. 5; CAPRYLOYL GLYCINE; PURSLANE; TEA TREE OIL; TREMELLA FUCIFORMIS WHOLE; MENTHA CANADENSIS WHOLE; TROLAMINE; HYDROXYACETOPHENONE; CARBOMER HOMOPOLYMER, UNSPECIFIED TYPE; HYDROXYETHYL CELLULOSE, UNSPECIFIED; GYNOSTEMMA PENTAPHYLLUM TOP; ISOHEXADECANE; SORBITAN MONOOLEATE; ATRACTYLODES MACROCEPHALA ROOT; SOPHORA FLAVESCENS ROOT; BUTYLENE GLYCOL; FORSYTHIA SUSPENSA FRUIT; KAEMPFERIA GALANGA ROOT; SORBITAN MONOSTEARATE; PEG-100 STEARATE; BIFIDOBACTERIUM ANIMALIS LACTIS; POLYSORBATE 60; DIMETHICONE; ETHYLHEXYLGLYCERIN; FRAGRANCE 13576; EDETATE DISODIUM; CHLORPHENESIN; ETHYLHEXYL PALMITATE; SHEA BUTTER; VINCETOXICUM ATRATUM STEM; GARDEN SNAIL MUCIN; 1,2-HEXANEDIOL; PANTHENOL; SODIUM ACRYLATE/SODIUM ACRYLOYLDIMETHYLTAURATE COPOLYMER (4000000 MW); CETOSTEARYL ALCOHOL; MINERAL OIL; PHENOXYETHANOL; FD&C BLUE NO. 1

Active ingredients

Niacinamide 100%

Purpose

our formula is enhanced with soothing
natural ingredients.it helps to soothe the breakouts and
irritation, clear the pores and fade acne scars ,helps to
hydrate the skin and protect it from possible drying.

Uses

Apply amount to face ,gently massage until
fully absorbed.

Warnings

Avoid contact with eyes or mouth

Dosage and administration

For external use only.

Do not use

Stop use and ask a doctor if

When using section

avoid contact with the eyes. in case of accidental contact, rinse eyes with large amounts of cool tap water

some people have experienced changes in hair color and/or texture

Keep out of reach of children.

If sxralowed, get medical help or contact a Poison Conirol Cenler ngiht away.

Inactive ingredients

Water
Glycerin
Mineral Oil
Ethylhexyl Palmitate
Polysorbate 60
Dimethicone
Sorbitan Stearate
Cetearyl Alcohol
Phenoxyethanol
Butyrospermum Parkii (Shea) Butter
PEG-100 Stearate
Glyceryl Stearate
Triethanolamine
Carbomer
Allantoin
Chlorphenesin
Ethylhexylglycerin
Hydroxyethylcellulose
Panthenol
Sodium Acrylate/Sodium Acryloyldimethyl Taurate Copolymer
Isohexadecane
Fragrance
Disodium EDTA
Polysorbate 80
Sorbitan Oleate
Sodium Chloride
CI 19140
Butylene Glycol
CI 42090
Capryloyl Glycine
Lactobacillus/Soy Milk Ferment Filtrate
Portulaca Oleracea Extract
Salix Alba (Willow) Bark Extract
Houttuynia Cordata Extract
Forsythia Suspensa Fruit Extract
Cynanchum Atratum Extract
Melaleuca Alternifolia (Tea Tree) Extract
Tremella Fuciformis (Mushroom) Extract
Kaempferia Galanga Root Extract
Mentha Haplocalyx Extract
Atractylodes Macrocephala Rhizome Extract
Pentylene Glycol
Sophora Angustifolia Root Extract
1,2-Hexanediol
Gynostemma Pentaphyllum Extract
Snail Secretion Filtrate
Hydroxyacetophenone

stop use

on broken or irritated scalp